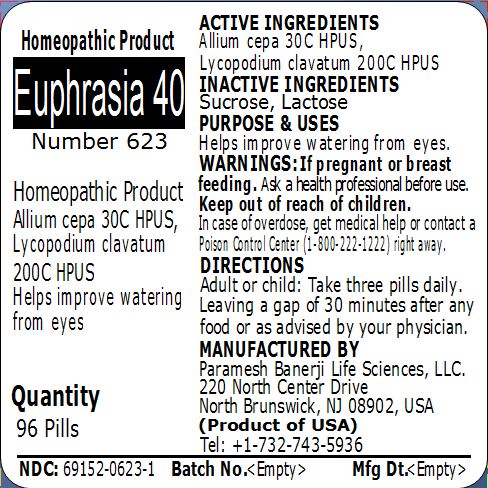 DRUG LABEL: Euphrasia 40 Number 623
NDC: 69152-0623 | Form: PELLET
Manufacturer: Paramesh Banerji Life Sciences LLC
Category: homeopathic | Type: HUMAN OTC DRUG LABEL
Date: 20150312

ACTIVE INGREDIENTS: ONION 30 [hp_C]/1 1; LYCOPODIUM CLAVATUM SPORE 200 [hp_C]/1 1
INACTIVE INGREDIENTS: LACTOSE; SUCROSE

Active Ingredients

Allium cepa 30C HPUS, Lycopodium clavatum 200C HPUS

Inactive Ingredients

Sucrose, Lactose

Purpose

Helps improve watering from eyes

Uses

Helps improve watering from eyes

Warnings

If pregnant or breast feeding ask a health professional before use.

Keep out of reach of children. In case of overdose, get medical help or contact a Poison Control Center (1-800-222-1222) right away.

Direction

Adult or child: Take three pills daily. Leaving a gap of 30 minutes after any food or as advised by your physician.

Manufactured by

Paramesh Banerji Life Sciences, LLC

220 North Center Drive

North Brunswick, NJ 08902, USA

Product of USA

Tel: +1-732-743-5936

Principal Display Panel

Homeopathic Product

Euphrasia 40

Number 623

Homeopathic Product

Allium cepa 30C HPUS, Lycopodium clavatum 200C HPUS

Helps improve watering from eyes

Quantity

96 Pills